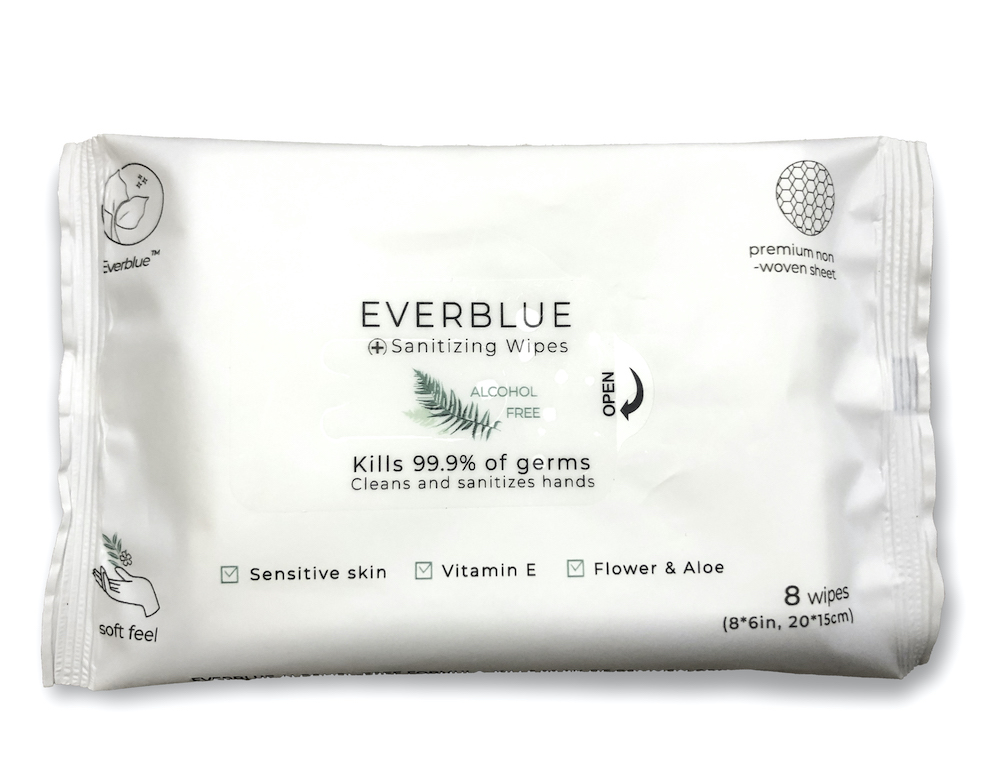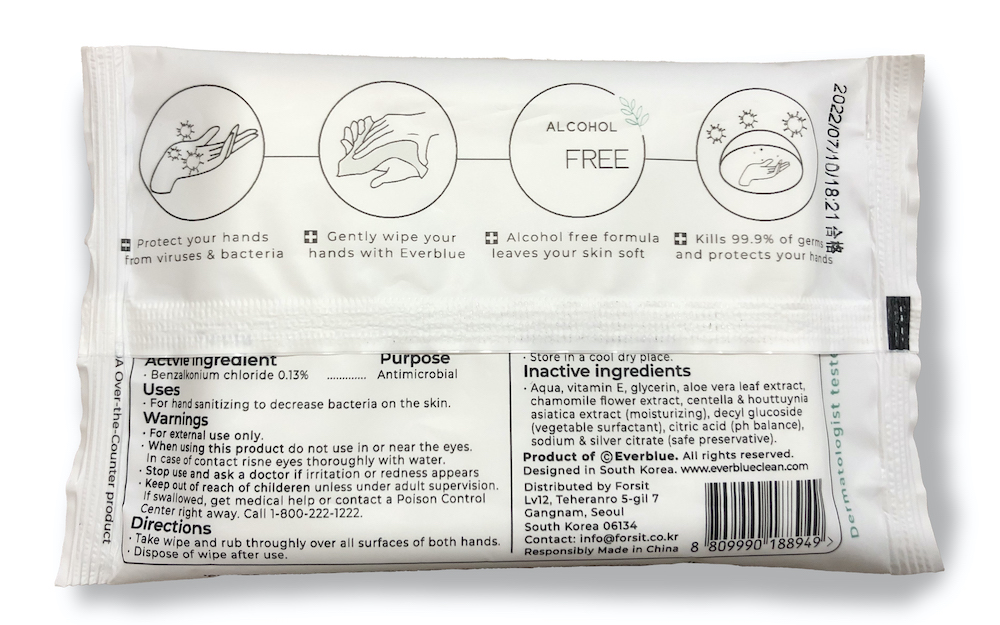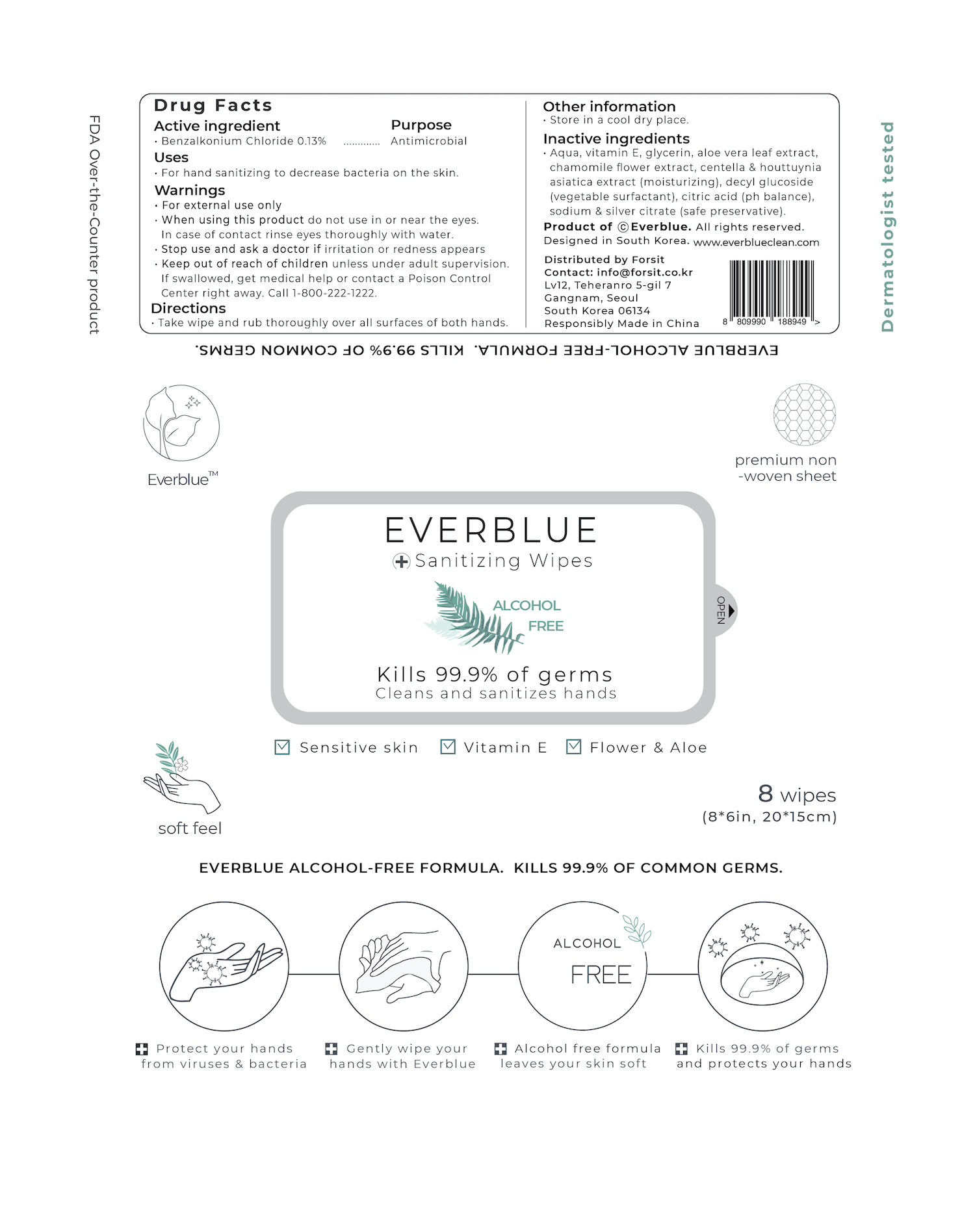 DRUG LABEL: Sanitizing Wipes
NDC: 79431-101 | Form: CLOTH
Manufacturer: Forsit
Category: otc | Type: HUMAN OTC DRUG LABEL
Date: 20200727

ACTIVE INGREDIENTS: BENZALKONIUM CHLORIDE 0.00013 mg/1 mg
INACTIVE INGREDIENTS: SILVER CITRATE; CENTELLA ASIATICA; DECYL GLUCOSIDE; SODIUM CITRATE; ALOE VERA LEAF; ALPHA-TOCOPHEROL; CHAMOMILE FLOWER OIL; ANHYDROUS CITRIC ACID; WATER; GLYCERIN

Everblue Alcohol Free Hand Sanitizing Wipes. 48pcs.

Active Ingredient(s)

• Benzalkonium Chloride 0.13% / Purpose: Antimicrobial

Purpose

Antimicrobial, Hand Sanitizer

Use

• For hand sanitizing to decrease bacteria on the skin.

Warnings

• For external use only
• When using this product do not use in or near the eyes. In case of contact, rinse eyes thoroughly with water.
• Stop use and ask a doctor if irritation or redness appears
• Keep out of reach of children unless under adult supervision.

• If swallowed, get medical help or contact Poison Control
Center right away. Call 1-800-222-1222.

Directions

• Take wipe and rub thoroughly over all surfaces of both hands.
• Dispose of wipe after use

• Keep out of reach of children unless under adult supervision.

Other information

• Store in a cool dry place.

Inactive ingredients

• Aqua, vitamin E, glycerin, aloe vera leaf extract, chamomile flower extract, centella & houttuynia, asiatica extract, decyl glucoside, citric acid, sodium citrate, silver citrate

Package Label - Principal Display Panel

48 wipes. NDC: 79431-101-06.